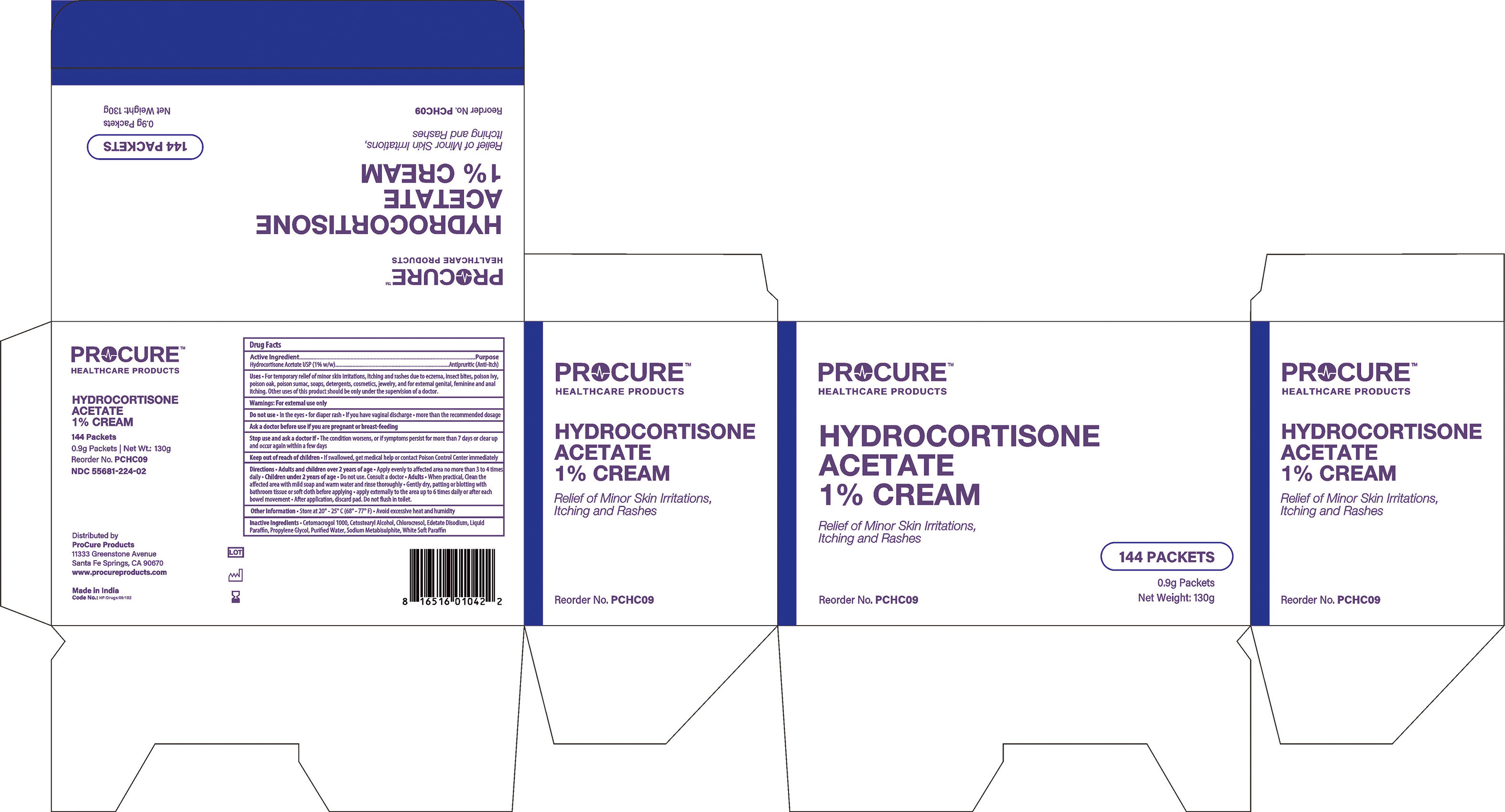 DRUG LABEL: procure
NDC: 55681-224 | Form: OINTMENT
Manufacturer: TWIN MED, LLC
Category: otc | Type: HUMAN OTC DRUG LABEL
Date: 20250620

ACTIVE INGREDIENTS: HYDROCORTISONE ACETATE 1 g/100 g
INACTIVE INGREDIENTS: CETETH-20; MINERAL OIL; PETROLATUM; CETOSTEARYL ALCOHOL; EDETATE SODIUM; PROPYLENE GLYCOL; WATER; SODIUM METABISULFITE; CHLOROCRESOL

Drug Facts

Active Ingredient (per gram)

Hydrocortisone Acetate, USP (1% w/w)

Purpose

Antipruritic (Anti-Itch)

Uses

For temporary relief of minor skin irritations, itching and rashes due to eczema, insect bites, poison ivy, poison oak, poison sumac, soaps, detergents, cosmetics, jewelry, and for external gential, feminine and anal itching. Other uses of this product should be only under the advice and supervision of a doctor.

Warnings

FOR EXTERNAL USE ONLY.

Do not use

- In the eyes
- for diaper rash
- if you have vaginal discharge
- more than recommended dosage.

Ask a doctor before use if

you are pregnant or breast feeding

Stop use and ask a doctor if

- the condition worsens, or if symptoms persists for more than 7 days or clear up and occur again within a few days.

Keep out of reach of children

If swallowed, get medical help or contact a Poison Control Center right away.

Directions

- Adults and children over 2 years of age
- Apply evenly to affected area no more than 3 to 4 times daily
- Children under 2 years of age
- Do not use, consult a doctor
- Adults- When practical, cleanse the affected area with mild soap and warm water and rinse thoroughly
- Gently dry, patting or blotting with bathroom tissue or soft cloth before applying
- apply externally to the area up to 6 times daily or after bowel movment
- After application, discard pad. Do not flush in toilet.

Other Information

- Store at 20o-25oC(68o-77oF)
- Avoid excessive heat and humidity.

Inactive Ingredients

Cetomacrogol 1000, Cetostearyl Alcohol, Chloracresol, Edetate Disodium, Liquid Paraffin, Propylene Glycol, Purified Water, Sodium Metabisulphite, White Soft Paraffin.